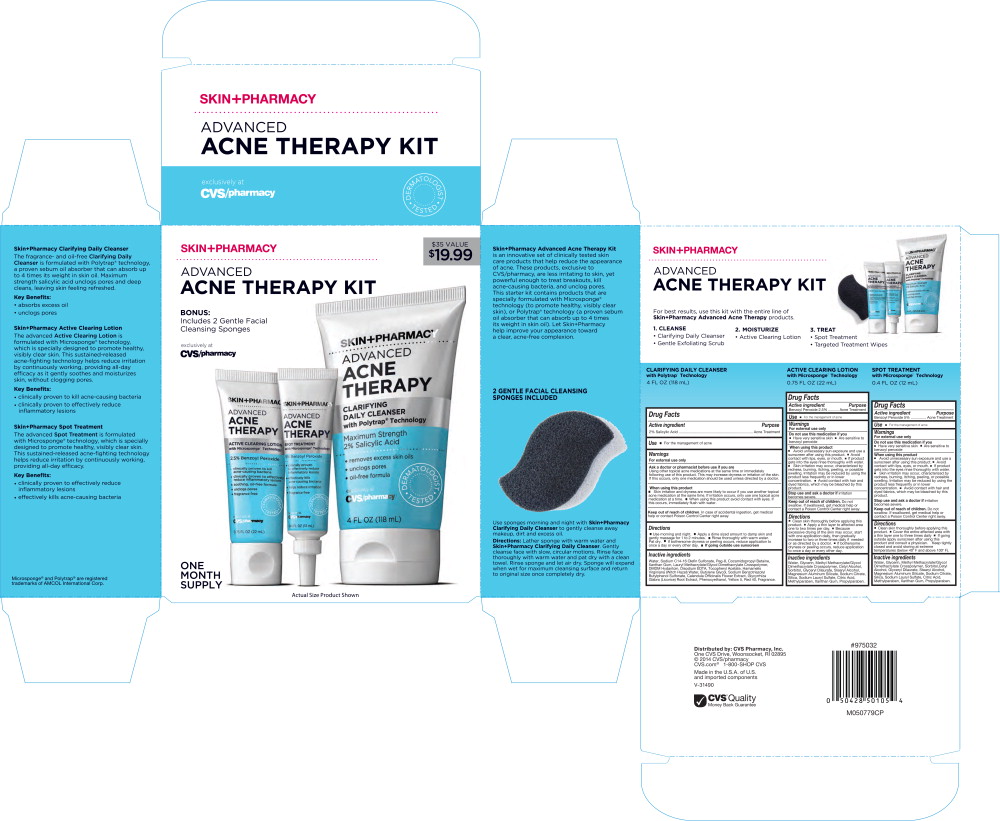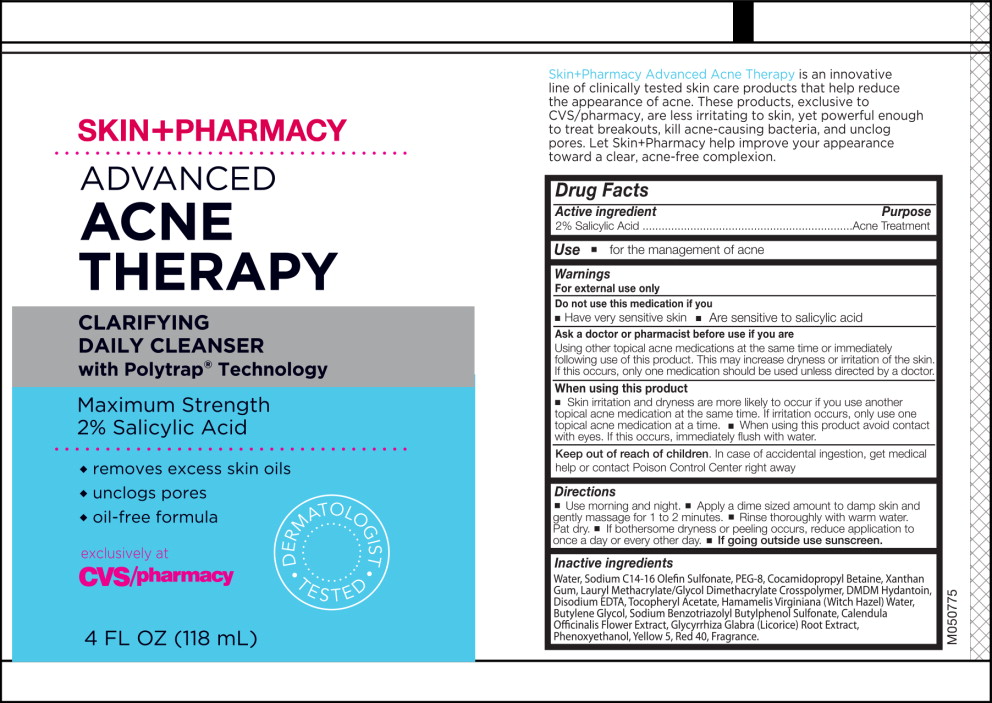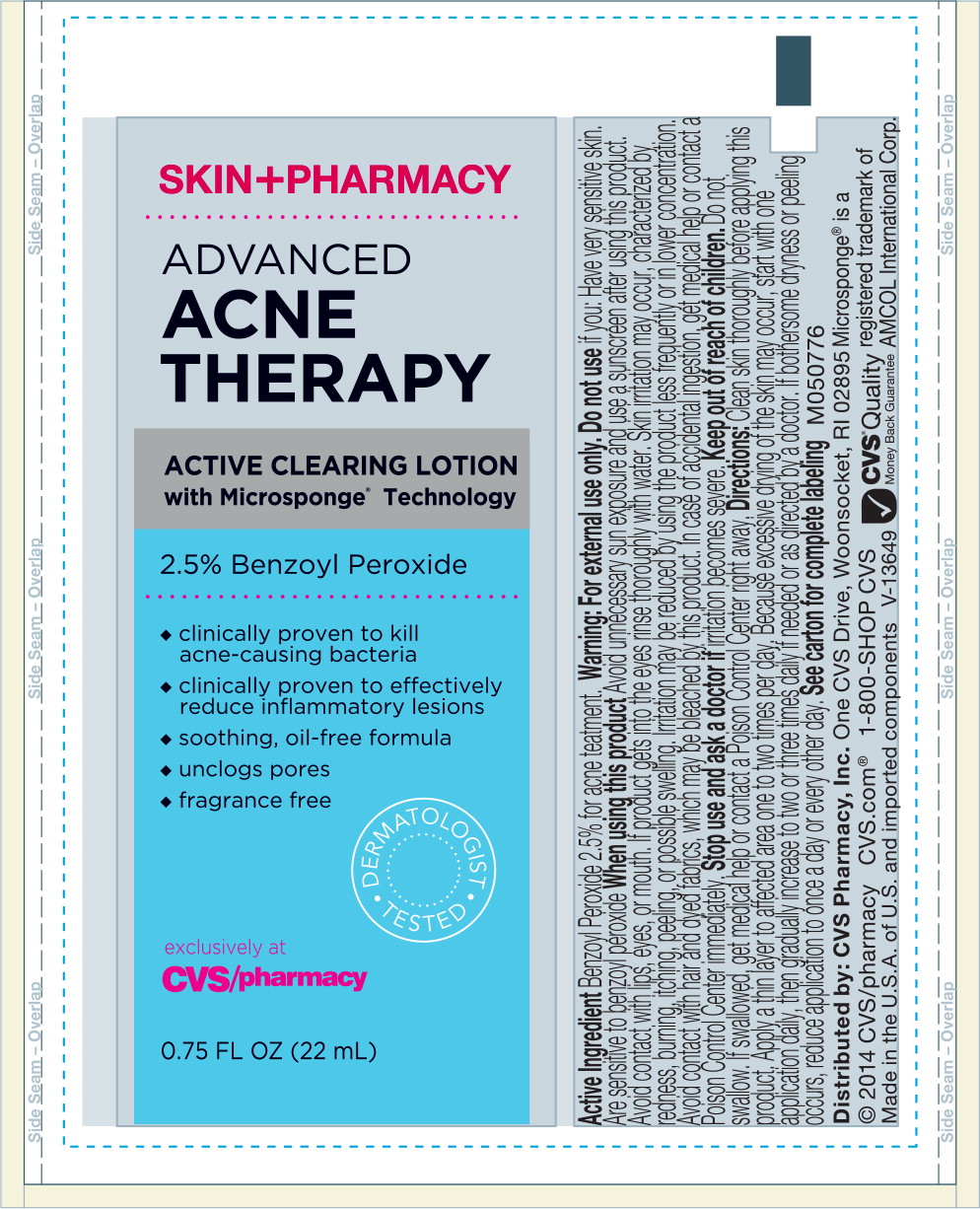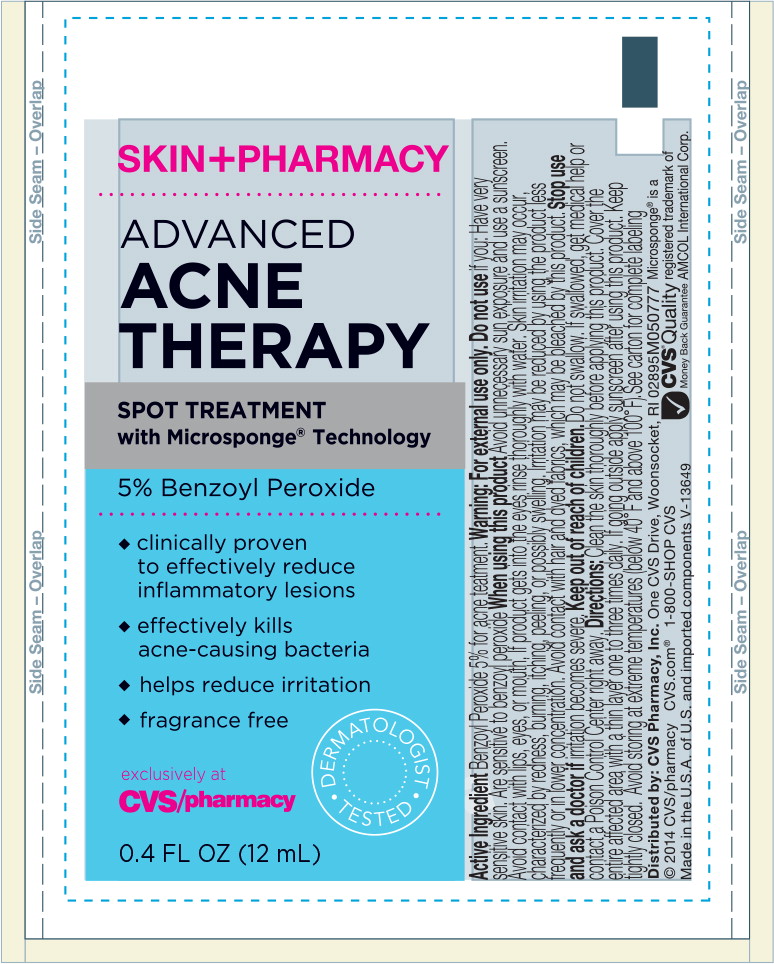 DRUG LABEL: SkinPharmacy Advanced Acne Therapy Kit
NDC: 69842-082 | Form: KIT | Route: TOPICAL
Manufacturer: CVS Health
Category: otc | Type: HUMAN OTC DRUG LABEL
Date: 20170314

ACTIVE INGREDIENTS: salicylic acid 20 mg/1 mL; benzoyl peroxide 25 mg/1 mL; benzoyl peroxide 50 mg/1 mL
INACTIVE INGREDIENTS: Water; sodium C14-16 olefin sulfonate; polyethylene glycol 4000; cocamidopropyl betaine; Xanthan gum; DMDM Hydantoin; edetate disodium; .alpha.-tocopherol acetate, DL-; Hamamelis virginiana flower water; Butylene glycol; Calendula Officinalis flower; licorice; Phenoxyethanol; FD&C Yellow No. 5; FD&C red no. 40; Lauryl Methacrylate/Glycol Dimethacrylate Crosspolymer; water; glycerin; methyl methacrylate/glycol dimethacrylate crosspolymer; cetyl alcohol; sorbitol; glyceryl dilaurate; stearyl alcohol; magnesium aluminum silicate; sodium citrate; silicon dioxide; sodium lauryl sulfate; citric acid monohydrate; methylparaben; xanthan gum; propylparaben; water; glycerin; methyl methacrylate/glycol dimethacrylate crosspolymer; cetyl alcohol; sorbitol; glyceryl dilaurate; stearyl alcohol; magnesium aluminum silicate; sodium citrate; silicon dioxide; sodium lauryl sulfate; citric acid monohydrate; methylparaben; xanthan gum; propylparaben

CLARIFYING DAILY CLEANSER with Polytrap® Technology

4 FL OZ (118 mL)

Drug Facts

Active Ingredient

2% Salicylic Acid

Purpose

Acne Treatment

Use

- For the management of acne

Warnings

For external use only

Ask a doctor or pharmacist before use if you are

Using other topical acne medications at the same time or immediately following use of this product. This may increase dryness or irritation of the skin. If this occurs, only one medication should be used unless directed by a doctor.

When using this product

- Skin irritation and dryness are more likely to occur if you use another topical acne medication at the same time. If irritation occurs, only use one topical acne medication at a time.
- When using this product avoid contact with eyes. If this occurs, immediately flush with water.

Keep out of reach of children. In case of accidental ingestion, get medical help or contact Poison Control Center right away.

Directions

- Use morning and night.
- Apply a dime sized amount to damp skin and gently massage for 1 to 2 minutes.
- Rinse thoroughly with warm water.
- Pat dry.
- If bothersome dryness or peeling occurs, reduce application to once a day or every other day.
- If going outside use sunscreen

Inactive ingredients

Water, Sodium C14-16 Olefin Sulfonate, Peg-8, Cocamidopropyl Betaine, Xanthan Gum, Lauryl Methacrylate/Glycol Dimethacrylate Crosspolymer, DMDM Hydantoin, Disodium EDTA, Tocopheryl Acetate, Hamamelis Virginiana (Witch Hazel) Water, Butylene Glycol, Sodium Benzotriazolyl Butylphenol Sulfonate, Calendula Officinalis Flower Extract, Glycyrrhiza Glabra (Licorice) Root Extract, Phenoxyethanol, Yellow 5, Red 40, Fragrance.

ACTIVE CLEARING LOTION with Microsponge® Technology

0.75 FL OZ (22 mL)

Drug Facts

Active Ingredient

Benzoyl Peroxide 2.5%

Purpose

Acne Treatment

Use

- for the management of acne

Warnings

For external use only

Do not use this medication if you

- Have very sensitive skin
- Are sensitive to benzoyl peroxide

When using this product

- Avoid unnecessary sun exposure and use a sunscreen after using this product.
- Avoid contact with lips, eyes, or mouth.
- If product gets into eyes rinse thoroughly with water.
- Skin irritation may occur, characterized by redness, burning, itching, peeling, or possible swelling. Irritation may be reduced by using the product less frequently or in lower concentration.
- Avoid contact with hair and dyed fabrics, which may be bleached by this product.

Stop use and ask a doctor if irritation becomes severe.

Keep out of reach of children. Do not swallow. If swallowed, get medical help or contact a Poison Control Center right away.

Directions

- Clean skin thoroughly before applying this product.
- Apply a thin layer to affected area one to two times per day.
- Because excessive drying of the skin may occur, start with one application daily, then gradually increase to two to three time daily if needed or as directed by a doctor.
- If bothersome dryness or peeling occurs, reduce application to once a day or every other day.

Inactive ingredients

Water, Glycerin, Methyl Methacrylate/Glycol Dimethacrylate Crosspolymer, Cetyl Alcohol, Sorbitol, Glyceryl Dilaurate, Stearyl Alcohol, Magnesium Aluminum Silicate, Sodium Citrate, Silica, Sodium Lauryl Sulfate, Citric Acid, Methylparaben, Xanthan Gum, Propylparaben.

SPOT TREATMENT with Microsponge® Technology

0.4 FL OZ (12 mL)

Drug Facts

Active Ingredient

Benzoyl Peroxide 5%

Purpose

Acne Treatment

Use

- for the management of acne

Warnings

For external use only

Do not use this medication if you

- Have very sensitive skin
- Are sensitive to benzoyl peroxide

When using this product

- Avoid unnecessary sun exposure and use a sunscreen after using this product.
- Avoid contact with lips, eyes, or mouth.
- If product gets into eyes rinse thoroughly with water.
- Skin irritation may occur, characterized by redness, burning, itching, peeling, or possible swelling. Irritation may be reduced by using the product less frequently or in lower concentration.
- Avoid contact with hair and dyed fabrics, which may be bleached by this product.

Stop use and ask a doctor if irritation becomes severe.

Keep out of reach of children. Do not swallow. If swallowed, get medical help or contact a Poison Control Center right away.

Directions

- Clean skin thoroughly before applying this product.
- Cover the entire affected area with a thin layer one to three times daily.
- If going outside apply sunscreen after using this product and consult a physician. Keep tightly closed and avoid storing at extreme temperatures (below 40°F and above 100°F).

Inactive ingredients

Water, Glycerin, Methyl Methacrylate/Glycol Dimethacrylate Crosspolymer, Sorbitol, Cetyl Alcohol, Glyceryl Dilaurate, Stearyl Alcohol, Magnesium Aluminum Silicate, Sodium Citrate, Silica, Sodium Lauryl Sulfate, Citric Acid, Methylparaben, Xanthan Gum, Propylparaben.

Distributed by: CVS Pharmacy, Inc.

One CVS Drive, Woonsocket, RI 02895

© 2014 CVS/pharmacy

CVS.com® 1-800-SHOP CVS

Made in the U.S.A. of U.S. and imported components

V-31490

CVS® Quality

Money Back Guarantee

#975032

M050779CP

Principal Display Panel - Carton Label

SKIN+PHARMACY

ADVANCED
ACNE THERAPY KIT

$35 VALUE

$19.99

BONUS:

Includes 2 Gentle Facial
Cleansing Sponges

exclusively at
CVS/pharmacy

ONE MONTH SUPPLY

Actual Size Product Shown

Principal Display Panel - Clarifying Daily Cleanser Tube Label

SKIN+PHARMACY

ADVANCED
ACNE
THERAPY

CLARIFYING
DAILY CLEANSER
with Polytrap® Technology

Maximum Strength

2% Salicylic Acid

- removes excess skin oils
- unclogs pores
- oil-free formula

DERMATOLOGIST TESTED

exclusively at
CVS/pharmacy

4 FL OZ (118 mL)

Principal Display Panel - Active Clearing Lotion Tube Label

SKIN+PHARMACY

ADVANCED
ACNE
THERAPY

ACTIVE CLEARING LOTION
with Microsponge® Technology

- clinically proven to kill acne-causing bacteria
- clinically proven to effectively reduce inflammatory lesions
- soothing, oil-free formula
- unclogs pores
- fragrance free

DERMATOLOGIST TESTED

exclusively at
CVS/pharmacy

0.75 FL OZ (22 mL)

Principal Display Panel - Spot Treatment Tube Label

SKIN+PHARMACY

ADVANCED
ACNE
THERAPY

SPOT TREATMENT
with Microsponge® Technology

5% Benzoyl Peroxide

- clinically proven to effectively reduce inflammatory lesions
- effectively kills acne-causing bacteria
- helps reduce irritation
- fragrance free

DERMATOLOGIST TESTED

exclusively at
CVS/pharmacy

0.4 FL OZ (12 mL)